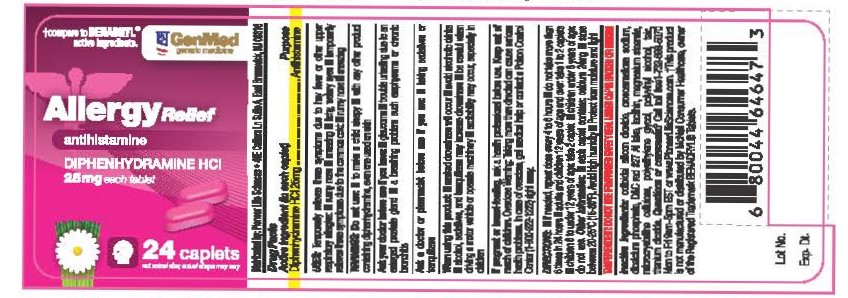 DRUG LABEL: Allergy Relief
NDC: 72090-021 | Form: TABLET
Manufacturer: Pioneer Life Sciences, LLC
Category: otc | Type: HUMAN OTC DRUG LABEL
Date: 20200701

ACTIVE INGREDIENTS: DIPHENHYDRAMINE HYDROCHLORIDE 25 mg/1 1
INACTIVE INGREDIENTS: LECITHIN, SOYBEAN; CELLULOSE, MICROCRYSTALLINE; CROSCARMELLOSE SODIUM; ANHYDROUS DIBASIC CALCIUM PHOSPHATE; SILICON DIOXIDE; MAGNESIUM STEARATE; POLYVINYL ALCOHOL, UNSPECIFIED; TALC; TITANIUM DIOXIDE; POLYETHYLENE GLYCOL, UNSPECIFIED; D&C RED NO. 27 ALUMINUM LAKE

Active Ingredient

Diphenhydramine Hcl 25mg

Purpose

Antihistamine

Uses:

temporarily relieves these symptoms due to hay fever or other upper respiratory allergies:

runny nose
sneezing
itchy, watery eyes
temporarily relieves these symptoms due to the common cold:
runny nose
sneezing

Warnings:

Do not use - to make a child sleepy - with any other product containing diphenhydramine, even one used on skin

Ask Doctor:

Ask a doctor before use if you have - glaucoma - troble urinating due to an enlarged prostate gland - a breathing problem such as emphysema or chronic bronchitis

ASK DOCTOR/PHARMACIST:

Ask a doctor or pharmacist before use if you aretaking sedatives or tranquilizers.

WHEN USING THIS PRODUCT

marked drowsiness may occur
avoid alcoholic drinks
alcohol, sedatives, and tranquilizers may increase drowsiness
be careful when driving a motor vehicle or operating machinery
excitability may occur, especially in children

PREGNANCY

If pregnant or breast-feeding, ask a health professional before use.

Keep out of reach of children. In case of overdose, get medical help or contact a Poison Control Center (1-800-222-1222) right away.

DIRECTIONS

if needed, repeat dose every 4 to 6 hours
do not take more than 6 times in 24 hours
adults and children 12 years of age or older - 1 to 2 caplets
children 6 to under 12 years - 1 caplet
children under 6 years of age - do not use.

OTHER INFORMATION

each tablets contains: calcium 24 mg - store between 20-25°C (68-77°F). Avoid high humidity. Protect from moisture and light

INACTIVE INGREDIENTS

Dicalcium phosphate, microcrystalline cellulose, croscarmellose sodium, colloidal silicon dioxide, magnesium stearate, OPADRY II

QUESTIONS OR COMMENTS?

Call 1-732-698-5070 Monday through Friday 9AM–5PM EST or www.pioneerlifesciences.com

PRINCIPAL DISPLAY PANEL

Label